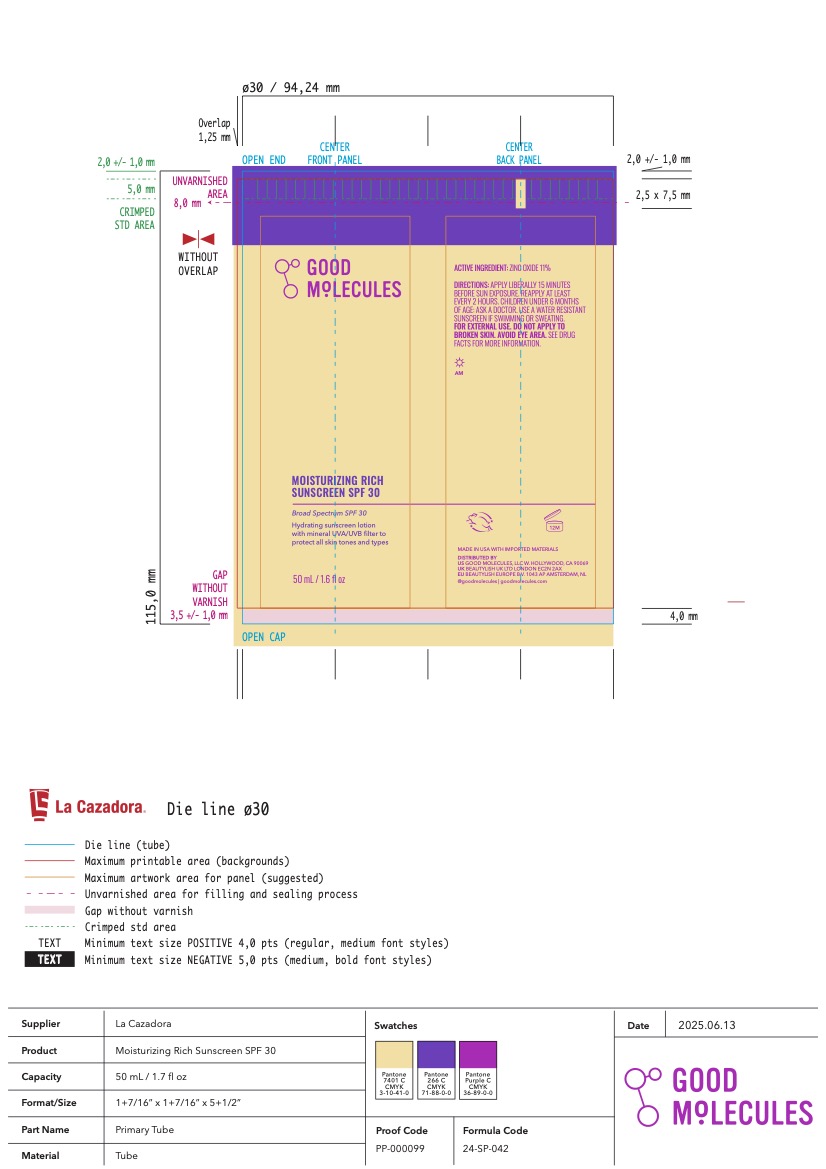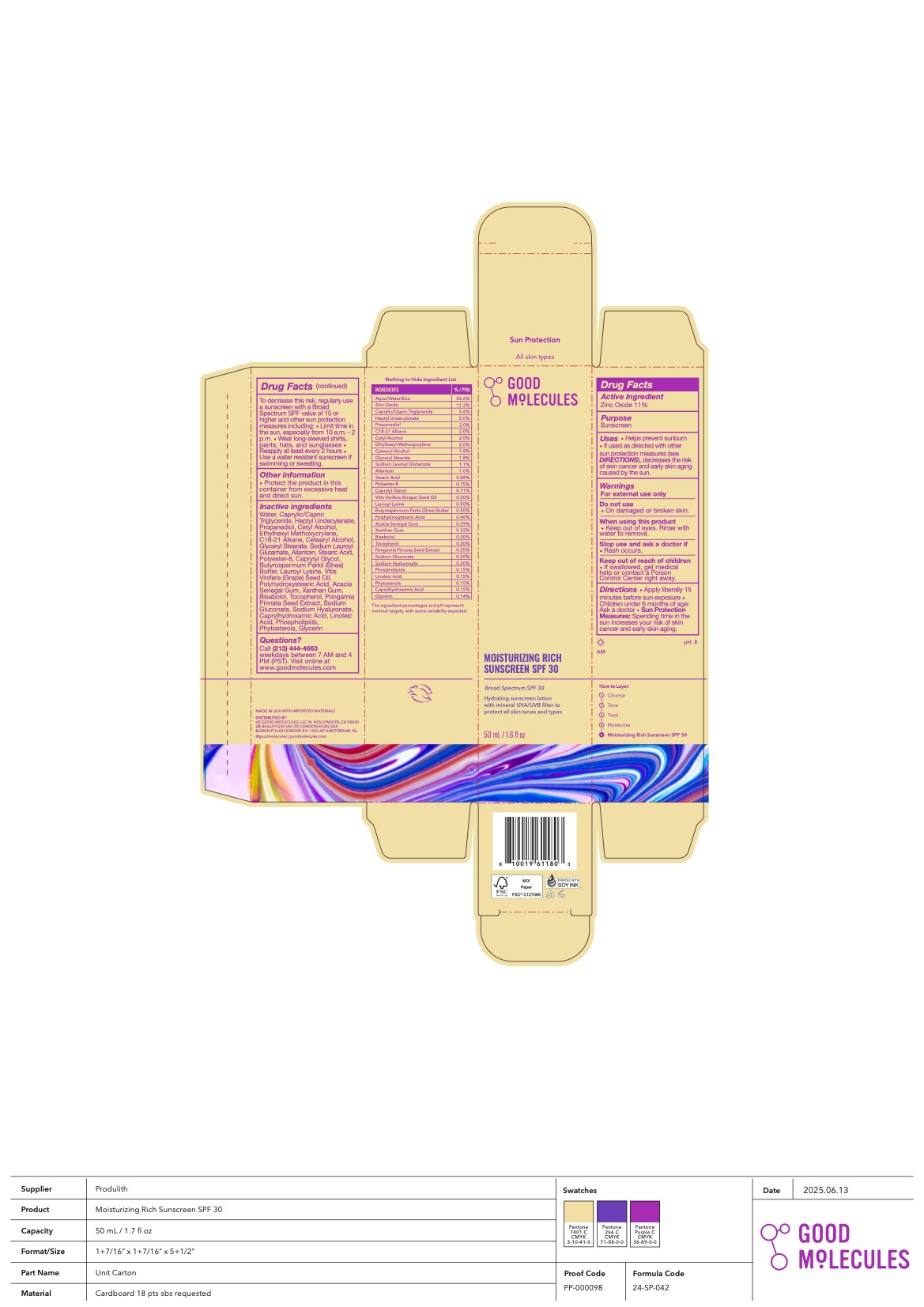 DRUG LABEL: Moisturizing Rich Sunscreen SPF 30
NDC: 82730-103 | Form: LOTION
Manufacturer: Good Molecules, LLC
Category: otc | Type: HUMAN OTC DRUG LABEL
Date: 20251001

ACTIVE INGREDIENTS: ZINC OXIDE 11.2 g/100 mL
INACTIVE INGREDIENTS: LECITHIN, SOYBEAN; VITIS VINIFERA (GRAPE) SEED OIL; PONGAMIA PINNATA SEED; HEPTYL UNDECYLENATE; WATER; XANTHAN GUM; BISABOLOL; SOY STEROL; SODIUM LAUROYL GLUTAMATE; POLYHYDROXYSTEARIC ACID (2300 MW); LINOLEIC ACID; CAPRYLHYDROXAMIC ACID; GLYCERIN; ALLANTOIN; STEARIC ACID; POLYESTER-8 (1400 MW, CYANODIPHENYLPROPENOYL CAPPED); CAPRYLYL GLYCOL; SODIUM HYALURONATE; CETYL ALCOHOL; ETHYLHEXYL METHOXYCRYLENE; OCTADECANE; GLYCERYL STEARATE; SODIUM GLUCONATE; LAUROYL LYSINE; BUTYROSPERMUM PARKII (SHEA) BUTTER; CAPRYLIC/CAPRIC TRIGLYCERIDE; PROPANEDIOL; CETEARYL ALCOHOL; ACACIA SENEGAL GUM; TOCOPHEROL

Good Molecules Moisturizing Rich Sunscreen SPF 30

ACTIVE INGREDIENT

Zinc Oxide - 11%

Purpose

Sunscreen

Uses

Helps prevent sunburn

If used as directed with other sun protection measures (see DIRECTIONS), decreases the risk of skin cancer and early skin aging caused by the sun.

Warnings

For external use only

Do not use on damaged or broken skin.

When using this product keep out of eyes. Rinse with water to remove.

Stop use and ask a doctor if rash occurs.

Keep out of reach of children

- If swallowed, get medical help or contact a Poison Control Center right away.

Directions

- Apply liberally 15 minutes before sun exposure
- Children under 6 months of age: Ask a doctor
- Sun Protection Measures: Spending time in the sun increases your risk of skin cancer and early skin aging. To decrease this risk, regularly use a sunscreen with a Broad Spectrum SPF value of 15 or higher and other sun protection measures including:
  - Limit time in the sun, especially from 10 a.m. - 2 p.m.
  - Wear long-sleeved shirts, pants, hats, and sunglasses
  - Reapply at least every 2 hours
  - Use a water resistant sunscreen if swimming or sweating.

Other information

- Protect the product in this container from excessive heat and direct sun.

INACTIVE INGREDIENT

Water, Caprylic/Capric Triglyceride, Heptyl Undecylenate, Propanediol, Cetyl Alcohol, Ethylhexyl Methoxycrylene, C18-21 Alkane, Cetearyl Alcohol, Glyceryl Stearate, Sodium Lauroyl Glutamate, Allantoin, Stearic Acid, Polyester-8, Caprylyl Glycol, Butyrospermum Parkii (Shea) Butter, Lauroyl Lysine, Vitis Vinifera (Grape) Seed Oil, Polyhydroxystearic Acid, Acacia Senegal Gum, Xanthan Gum, Bisabolol, Tocopherol, Pongamia Pinnata Seed Extract, Sodium Gluconate, Sodium Hyaluronate, Caprylhydroxamic Acid, Linoleic Acid, Phospholipids, Phytosterols, Glycerin

Questions?

Call (213) 444-4663 weekdays between 7 AM and 4 PM (PST). Visit online at www.goodmolecules.com